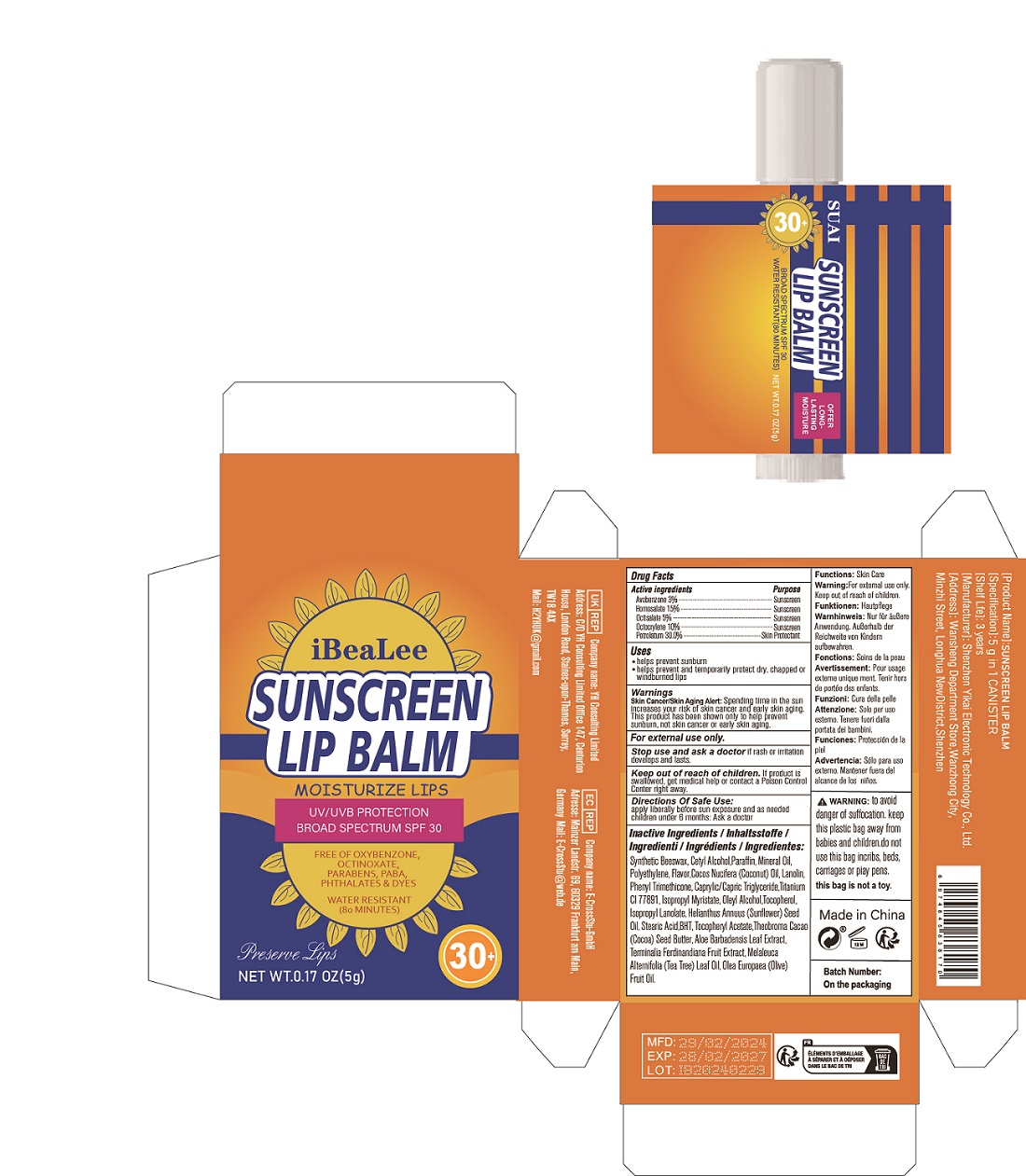 DRUG LABEL: SUNSCREEN LIP BALM
NDC: 84117-004 | Form: OINTMENT
Manufacturer: Shenzhen Hengkaifeng Commerce and Trade Co., Ltd
Category: otc | Type: HUMAN OTC DRUG LABEL
Date: 20240328

ACTIVE INGREDIENTS: AVOBENZONE 3 g/100 g; OCTISALATE 5 g/100 g; OCTOCRYLENE 10 g/100 g; HOMOSALATE 15 g/100 g; PETROLATUM 30 g/100 g
INACTIVE INGREDIENTS: SYNTHETIC BEESWAX; PARAFFIN; CETYL ALCOHOL

ACTIVE INGREDIENT

Avobenzone 3%

Homosalate 15%

Octisalate 5%

Octocrylene 10%

Petrolatum 30%

Purpose

Sunscreen
Skin Protectant

Use

helps prevent sunburn
helps prevent and temporarily protect dry, chapped or
windburned lips

WarningS

Skin Cancer/Skin Aging Alert: Spending time in the sun
increases your risk of skin cancer and early skin aging.
This product has been shown only to help prevent
sunburn, not skin cancer or early skin aging.

For external use only.

Stop use and ask a doctor

if rash or irritation develops and lasts.

Keep out of reach of children

If product is swallowed, get medical help or contact a Poison Control
Center right away.

Directions Of Safe Use

apply liberally before sun exposure and as needed
children under 6 months: Ask a doctor

Inactive ingredients

ynthetic Beeswax, Cetyl Alcohol,Paraffin, Mineral Oil,
Polyethylene, Flavor,Cocos Nucifera (Coconut) Oil, Lanolin,
Phenyl Trimethicone, Caprylic/Capric Triglyceride,Titanium
CI 77891, Isopropyl Myristate, Oleyl Alcohol,Tocopherol,
Isopropyl Lanolate, Helianthus Annuus (Sunflower) Seed
Oil, Stearic Acid,BHT, Tocopheryl Acetate,Theobroma Cacao
(Cocoa) Seed Butter, Aloe Barbadensis Leaf Extract,
Terminalia Ferdinandiana Fruit Extract, Melaleuca
Alternifolia (Tea Tree) Leaf Oil, Olea Europaea (Olive)
Fruit Oil.